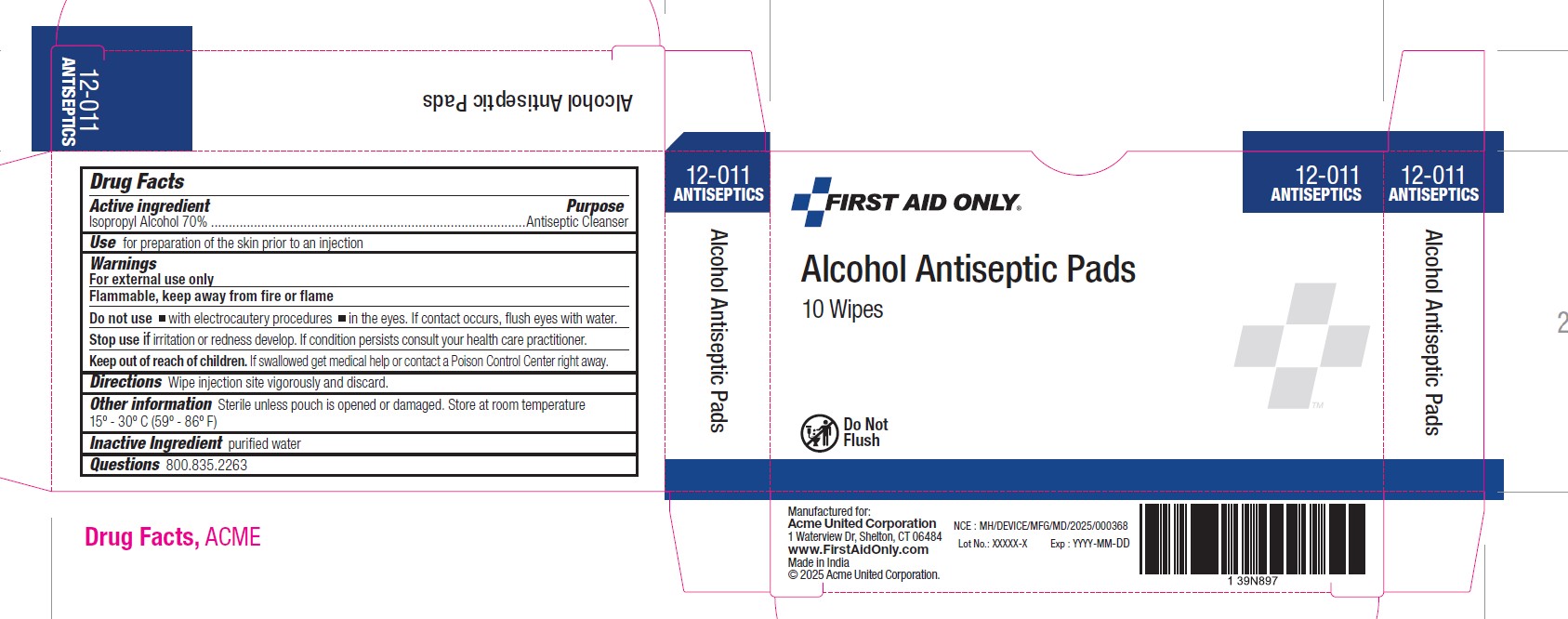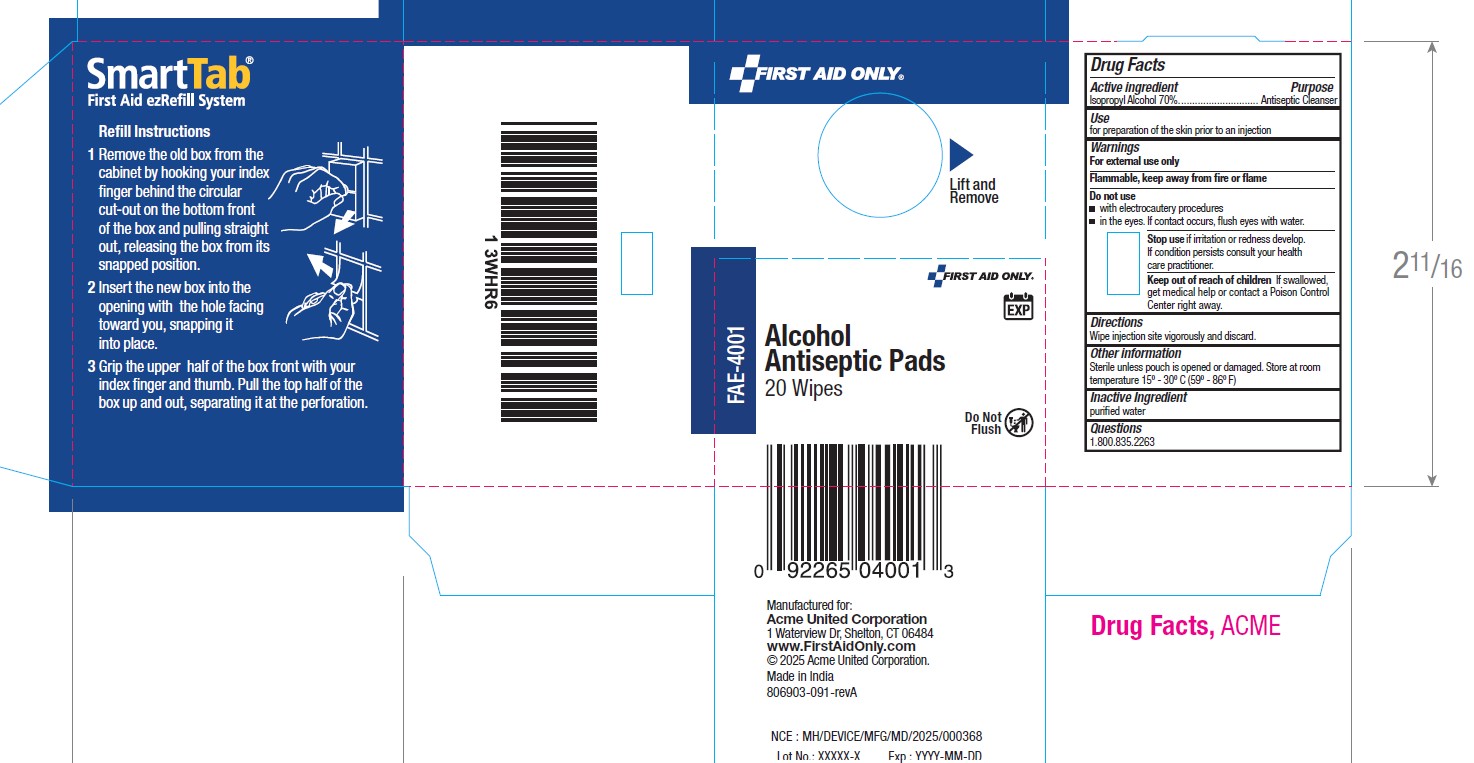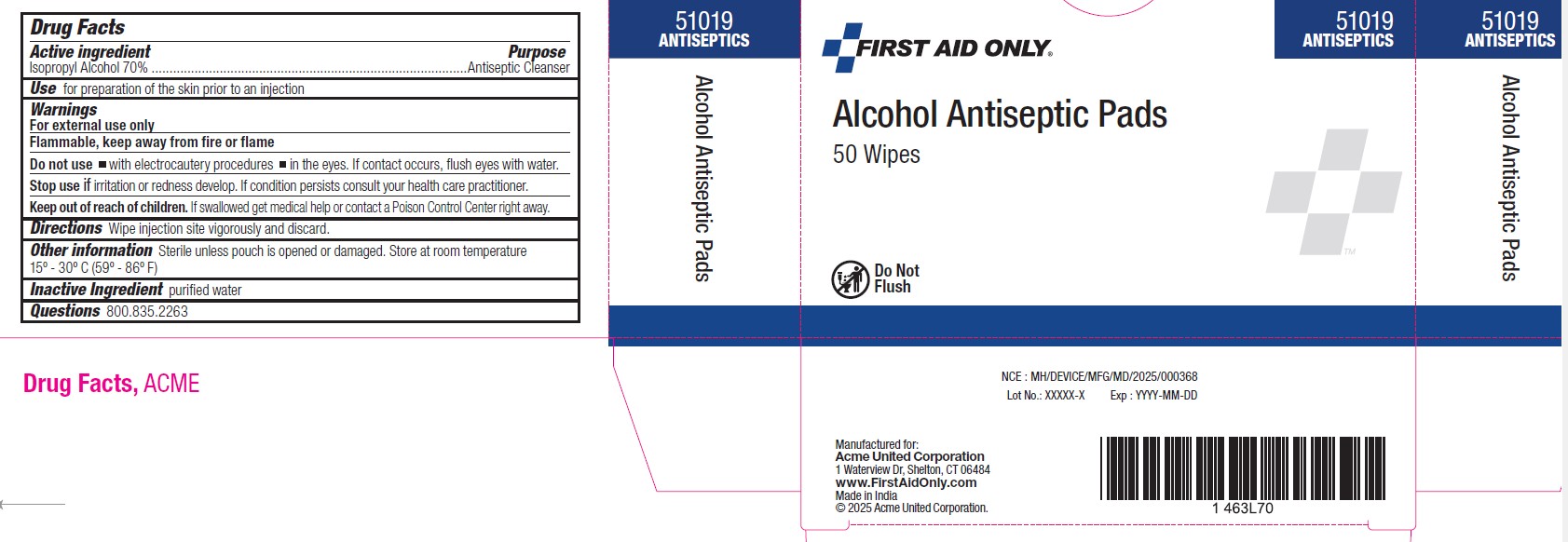 DRUG LABEL: Alcohol Prep Pads
NDC: 60913-048 | Form: SWAB
Manufacturer: Phoenix Healthcare Solutions LLC
Category: otc | Type: HUMAN OTC DRUG LABEL
Date: 20251023

ACTIVE INGREDIENTS: ISOPROPYL ALCOHOL 70 mL/100 mL
INACTIVE INGREDIENTS: WATER

Acme APP

Active Ingredients

Isopropyl alcohol 70% v/v

Purpose

Antiseptic Cleanser

Use

For preparation of the skin prior to injection

Warnings

For external use only. Flammable; keep away from fire and flame.

OTC - KEEP OUT OF REACH OF CHILDREN SECTION

If swallowed, get medical help or contact a Poison Control Center immediately.

Do not use

with electrocautery procedures, in the eyes, if contact occurs, flush eyes with water.

Directions

Wipe injection site vigorously.

Other information

Store at room temperature

Inactive Ingredient Section

Water